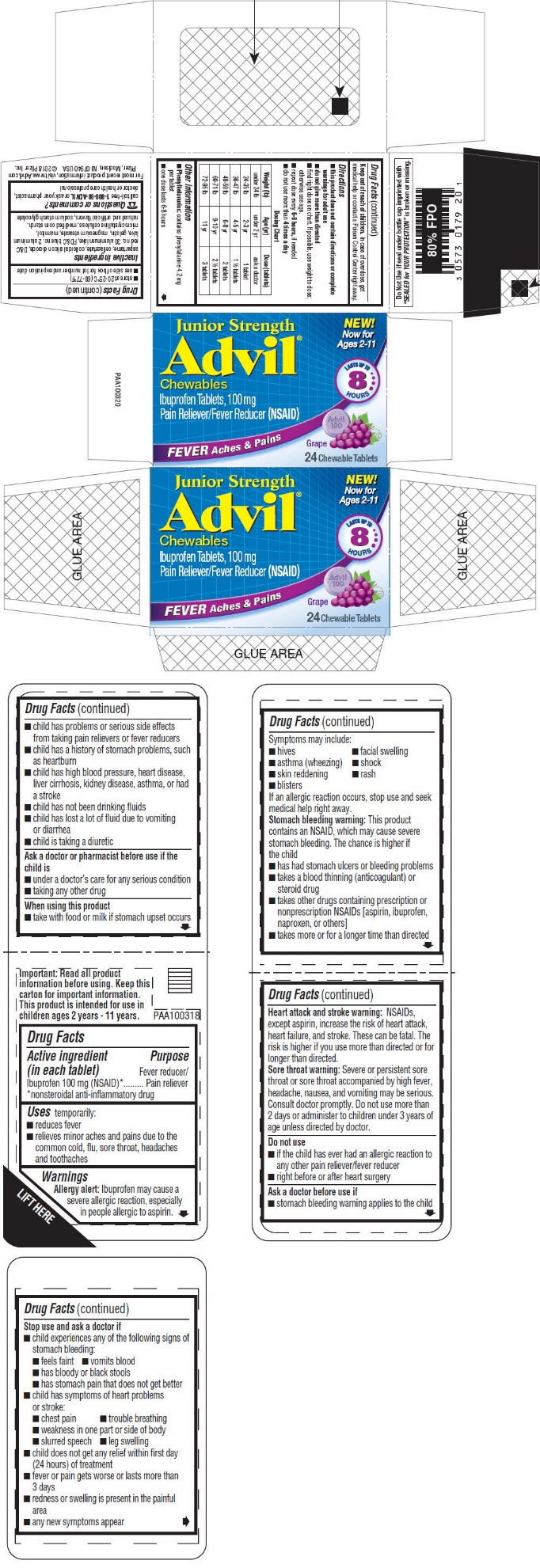 DRUG LABEL: JUNIOR STRENGTH ADVIL
NDC: 0573-0179 | Form: TABLET, CHEWABLE
Manufacturer: Haleon US Holdings LLC
Category: otc | Type: HUMAN OTC DRUG LABEL
Date: 20250627

ACTIVE INGREDIENTS: IBUPROFEN 100 mg/1 1
INACTIVE INGREDIENTS: ASPARTAME; CELLACEFATE; SILICON DIOXIDE; D&C RED NO. 30; FD&C BLUE NO. 2; GELATIN, UNSPECIFIED; MAGNESIUM STEARATE; MANNITOL; MICROCRYSTALLINE CELLULOSE; SODIUM STARCH GLYCOLATE TYPE A POTATO

Drug Facts

ACTIVE INGREDIENT (IN EACH TABLET)

Ibuprofen 100 mg (NSAID)*

*nonsteroidal anti-inflammatory drug

PURPOSE

Fever reducer/Pain reliever

USES

temporarily:

- reduces fever
- relieves minor aches and pains due to the common cold, flu, sore throat, headaches and toothaches

WARNINGS

Allergy alert:

Ibuprofen may cause a severe allergic reaction, especially in people allergic to aspirin. Symptoms may include:

- hives
- facial swelling
- asthma (wheezing)
- shock
- skin reddening
- rash
- blisters

If an allergic reaction occurs, stop use and seek medical help right away.

Stomach bleeding warning:

This product contains an NSAID, which may cause severe stomach bleeding. The chance is higher if the child

- has had stomach ulcers or bleeding problems
- takes a blood thinning (anticoagulant) or steroid drug
- takes other drugs containing prescription or nonprescription NSAIDs [aspirin, ibuprofen, naproxen, or others]
- takes more or for a longer time than directed

Heart attack and stroke warning

NSAIDs, except aspirin, increase the risk of heart attack, heart failure, and stroke. These can be fatal. The risk is higher if you use more than directed or for longer than directed.

Sore throat warning:

Severe or persistent sore throat or sore throat accompanied by high fever, headache, nausea, and vomiting may be serious. Consult doctor promptly. Do not use more than 2 days or administer to children under 3 years of age unless directed by doctor.

Do not use

- if the child has ever had an allergic reaction to any other pain reliever/fever reducer
- right before or after heart surgery

Ask a doctor before use if

- stomach bleeding warning applies to the child
- child has problems or serious side effects from taking pain relievers or fever reducers
- child has a history of stomach problems, such as heartburn
- child has high blood pressure, heart disease, liver cirrhosis, kidney disease, asthma, or had a stroke
- child has not been drinking fluids
- child has lost a lot of fluid due to vomiting or diarrhea
- child is taking a diuretic

Ask a doctor or pharmacist before use if the child is

- under a doctor's care for any serious condition
- taking any other drug

When using this product

- take with food or milk if stomach upset occurs

Stop use and ask a doctor if

- child experiences any of the following signs of stomach bleeding:
  - feels faint
  - vomits blood
  - has bloody or black stools
  - has stomach pain that does not get better
- child has symptoms of heart problems or stroke:
  - chest pain
  - trouble breathing
  - weakness in one part or side of body
  - slurred speech
  - leg swelling
- child does not get any relief within first day (24 hours) of treatment
- fever or pain gets worse or lasts more than 3 days
- redness or swelling is present in the painful area
- any new symptoms appear

Keep out of reach of children.

In case of overdose, get medical help or contact a Poison Control Center right away.

DIRECTIONS

- this product does not contain directions or complete warnings for adult use
- do not give more than directed
- find right dose on chart. If possible, use weight to dose; otherwise use age.
- repeat dose every 6-8 hours, if needed
- do not use more than 4 times a day

Dosing Chart
Weight (lb) | Age (yr) | Dose (tablets)
under 24 lb | under 2 yr | ask a doctor
24-35 lb | 2-3 yr | 1 tablet
36-47 lb | 4-5 yr | 1 ½ tablets
48-59 lb | 6-8 yr | 2 tablets
60-71 lb | 9-10 yr | 2 ½ tablets
72-95 lb | 11 yr | 3 tablets

OTHER INFORMATION

- Phenylketonurics: contains phenylalanine 4.2 mg per tablet
- one dose lasts 6-8 hours
- store at 20-25°C (68-77°F)
- see side of box for lot number and expiration date

INACTIVE INGREDIENTS

aspartame, cellacefate, colloidal silicon dioxide, D&C red no. 30 aluminum lake, FD&C blue no. 2 aluminum lake, gelatin, magnesium stearate, mannitol, microcrystalline cellulose, modified corn starch, natural and artificial flavors, sodium starch glycolate

QUESTIONS OR COMMENTS?

call toll-free 1-800-88-ADVIL or ask your pharmacist, doctor or health care professional

PRINCIPAL DISPLAY PANEL

Junior Strength
Advil®
Chewables
Ibuprofen Tablets, 100 mg
Pain Reliever/Fever Reducer (NSAID)

FEVER Aches & Pains

NEW!
Now for
Ages 2-11

LASTS UP TO
8
HOURS

Grape

24 Chewable Tablets